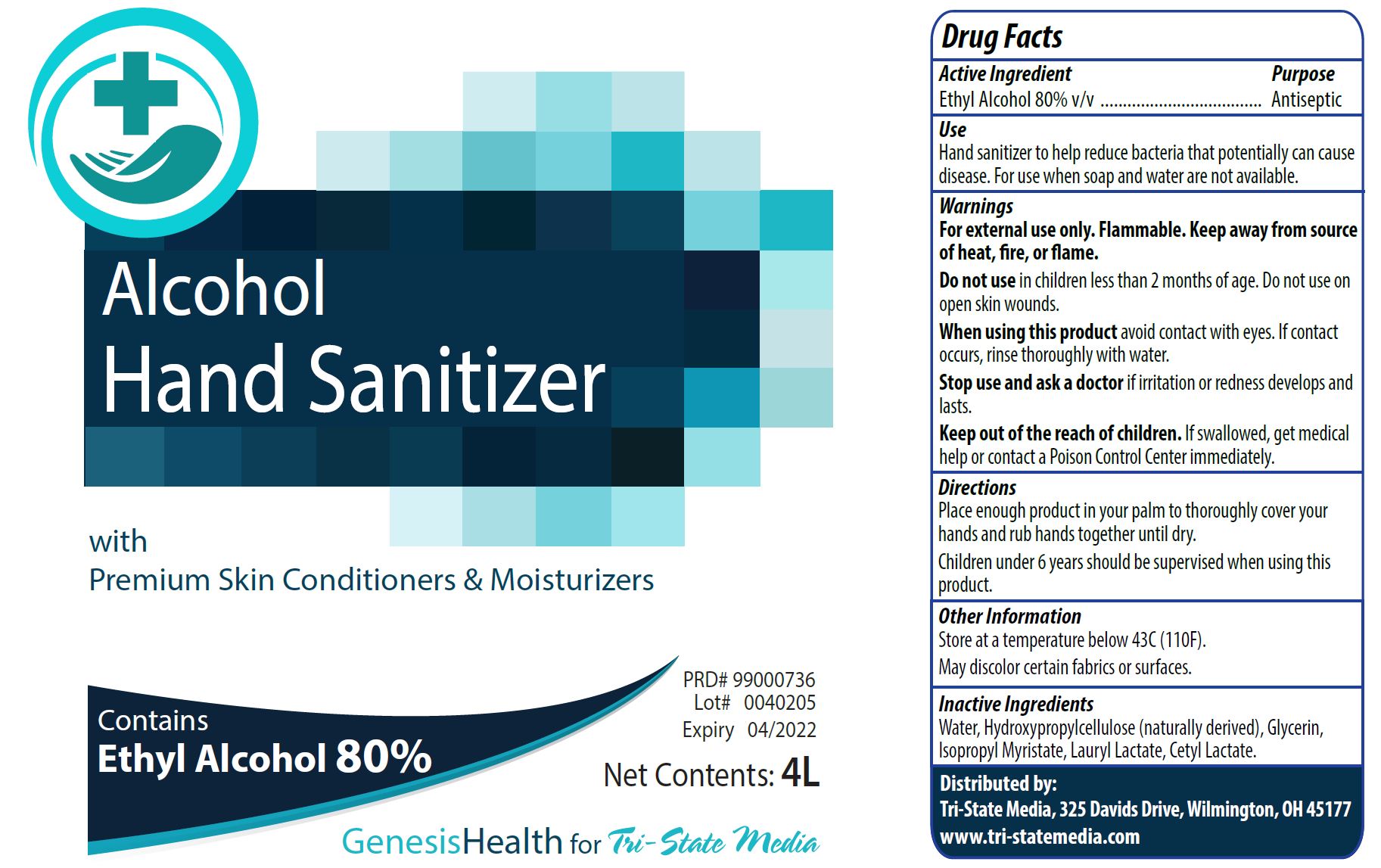 DRUG LABEL: Alcohol Hand Sanitizer
NDC: 75784-001 | Form: SOLUTION
Manufacturer: Tri-State Media, LLC
Category: otc | Type: HUMAN OTC DRUG LABEL
Date: 20200427

ACTIVE INGREDIENTS: ALCOHOL 80 L/100 L
INACTIVE INGREDIENTS: LAURYL LACTATE; ISOPROPYL MYRISTATE; CETYL LACTATE; HYDROXYPROPYL CELLULOSE, UNSPECIFIED; GLYCERIN; WATER

Active ingredient

Ethyl Alcohol 80% v/v

Purpose

Antiseptic

Uses

Hand sanitizer to help reduce bacteria that potentially can cause disease.

For use when soap and water are not available.

Warnings

For external use only. Flammable. Keep away from source of heat, fire, or flame.

Do not use in children less than 2 months of age. Do not use on open skin wounds.

When using this product avoid contact with eyes. If contact occurs, rinse thoroughly with water

Stop use and ask a doctor if irritation or redness develops and lasts.

KEEP OUT OF REACH OF CHILDREN

Keep out of the reach of children. If swallowed, get medical help or contact a Poison Control Center immediately.

Directions

Place enough product in your palm to thoroughly cover your hands and rub hands together until dry.

Children under 6 years should be supervised when using this product.

Other information

Store at a temperature below 43C (110F).

May discolor certain fabrics or surfaces.

Inactive ingredients

Water, Hydroxypropylcellulose (naturally derived), Glycerin, Isopropyl Myristate, Lauryl Lactate, Cetyl Lactate.

PACKAGE LABEL

Alcohol

Hand Sanitizer

with

Premium Skin Conditioners and Moisturizers

Contains

Ethyl Alcohol 80%

PRD# 99000736

Lot# 0040205

Expiry 04/2022

Net Contents: 4L

GenesisHealth